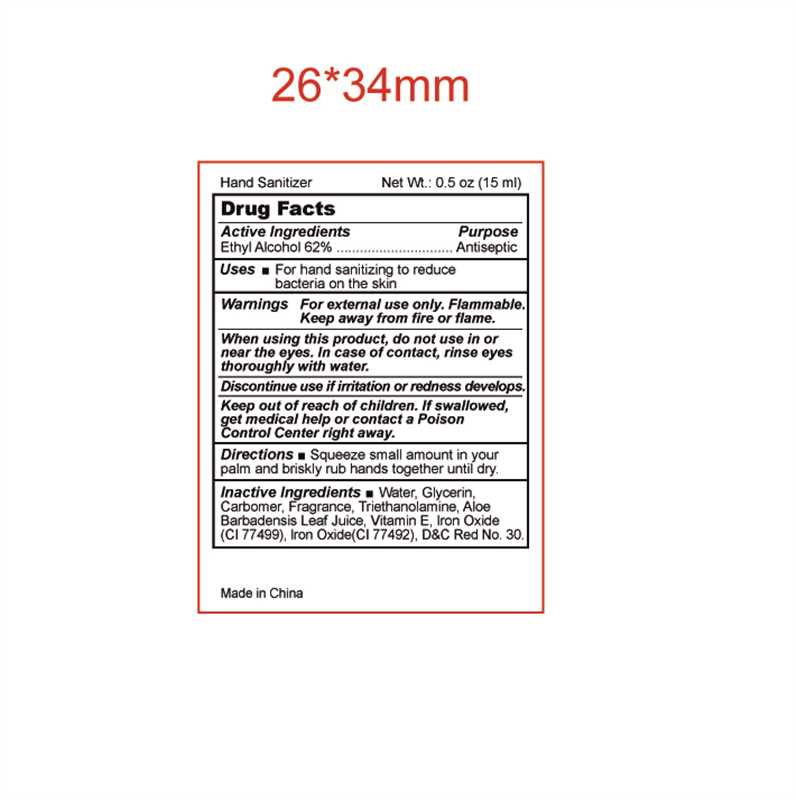 DRUG LABEL: Hand Sanitizer
NDC: 84641-006 | Form: GEL
Manufacturer: NANTONG QINJI HEALTH TECHNOLOGY CO., LTD.
Category: otc | Type: HUMAN OTC DRUG LABEL
Date: 20250617

ACTIVE INGREDIENTS: ALCOHOL 62 g/112 mL
INACTIVE INGREDIENTS: FERROSOFERRIC OXIDE; .ALPHA.-TOCOPHEROL; WATER; TROLAMINE; ALOE VERA LEAF; GLYCERIN; D&C RED NO. 30; FERRIC OXIDE YELLOW; CARBOMER INTERPOLYMER TYPE B (ALLYL PENTAERYTHRITOL CROSSLINKED)

84641-006-01

Active ingredients

Ethyl Alcohol 62%

Purpose

Antiperspirant

Use

For hand sanitizing to reduce bacteria on the skin

Warnings

For external use only. Flammable.

Keep away from fire or flame.

When using this produce,

do not use in or near the eyes. In case of contact, rinse eyes thoroughly with water.

discontinue use if

irritation or redness develops

Keep out of children.

If swallowed, get medical help or contact a Poison Control Center right away.

Directions

Squeeze small amount in your palm and briskly rub hands together until dry.

Inactive ingredients

Water, Glycerin, Carbomer, Fragrance, Triethanolamine, Aloe Barbadensis Leaf Juice, Vitamin E, Iron Oxide (CI 77499), Iron Oxide (CI 77492), D&C Red No.30.